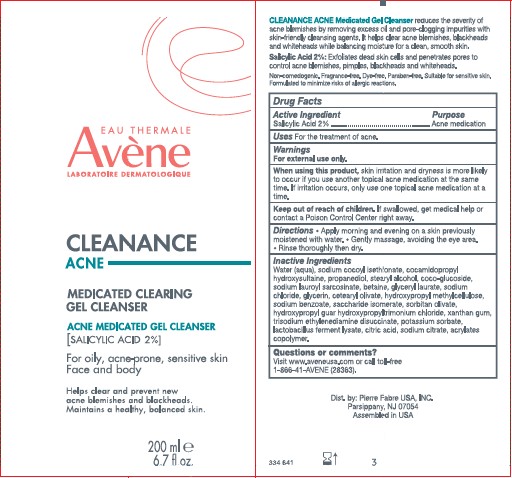 DRUG LABEL: Avene Cleanance Acne Medicated Clearing Gel Cleanser
NDC: 64760-775 | Form: LIQUID
Manufacturer: Pierre Fabre USA Inc.
Category: otc | Type: HUMAN OTC DRUG LABEL
Date: 20241106

ACTIVE INGREDIENTS: SALICYLIC ACID 2 mg/200 mL
INACTIVE INGREDIENTS: PROPANEDIOL; CETEARYL OLIVATE; WATER; COCAMIDOPROPYL HYDROXYSULTAINE; COCO GLUCOSIDE; SODIUM LAUROYL SARCOSINATE; BETAINE; HYPROMELLOSE, UNSPECIFIED; SODIUM BENZOATE; SACCHARIDE ISOMERATE; SORBITAN OLIVATE; HYDROXYPROPYL GUAR (2500-4500 MPA.S AT 1%); XANTHAN GUM; TRISODIUM ETHYLENEDIAMINE DISUCCINATE; POTASSIUM SORBATE; CITRIC ACID MONOHYDRATE; SODIUM CITRATE; ACRYLATES CROSSPOLYMER-6; SODIUM COCOYL ISETHIONATE; LIMOSILACTOBACILLUS FERMENTUM; STEARYL ALCOHOL; GLYCERIN; GLYCERYL LAURATE; SODIUM CHLORIDE

Avene Cleanance Acne Medicated Clearing Gel Cleanser

Purpose

Acne Medication

Active Ingredient

Salicylic Acid 2%

Uses

For the treatment of acne.

Warnings

For external use only.

When using this product

Skin irritation and dryness is more likely to occur if you use another topical acne medication at the same time. If irritation occurs, only use one topical acne medication at a time.

When using this product

If swallowed, get medical help or contact a Poison Control Center right away.

Directions

Apply morning and evening on a skin previously moistened with water.

Gently massage, avoiding the eye area.

Rinse thoroughly then dry.

Inactive Ingredients

Water (aqua), sodium cocoyl isethionate, cocamidopropyl hydroxysultaine, propanediol, stearyl alcohol, coco-glucoside, sodium lauroyl sarcosinate, betaine, glyceryl laurate, sodium chloride, glycerin, cetearyl olivate, hydroxypropyl methylcellulose, sodium benzoate, saccharide isomerate, sorbitan olivate, hydroxypropyl guar hydroxypropyltrimonium chloride, xanthan gum, trisodium ethylenediamine disuccinate, potassium sorbate, lactobacillus ferment lysate, citric acid, sodium citrate, acrylates copolymer

Questions or comments?

Visit www.aveneusa.com or call toll-free

1-866-41-AVENE (28363)

Package Label

EAU THERMALE

Avene

LABORATORIE DERMATOLOGIQUE

CLEANANCE

ACNE

MEDICATED CLEARING GEL CLEANSER

ACNE MEDICATED GEL CLEANER [SALICYLIC ACID 2%]

FOR OILY, ACNE-PRONE, SENSITIVE SKIN

FACE AND BODY

HELPS CLEAR AND PREVENT NEW ACNE BLEMISHES AND BLACKHEADS.

MAINTAINS A HEALTHY, BALANCED SKIN.

200 ML

6.7 FL. OZ.